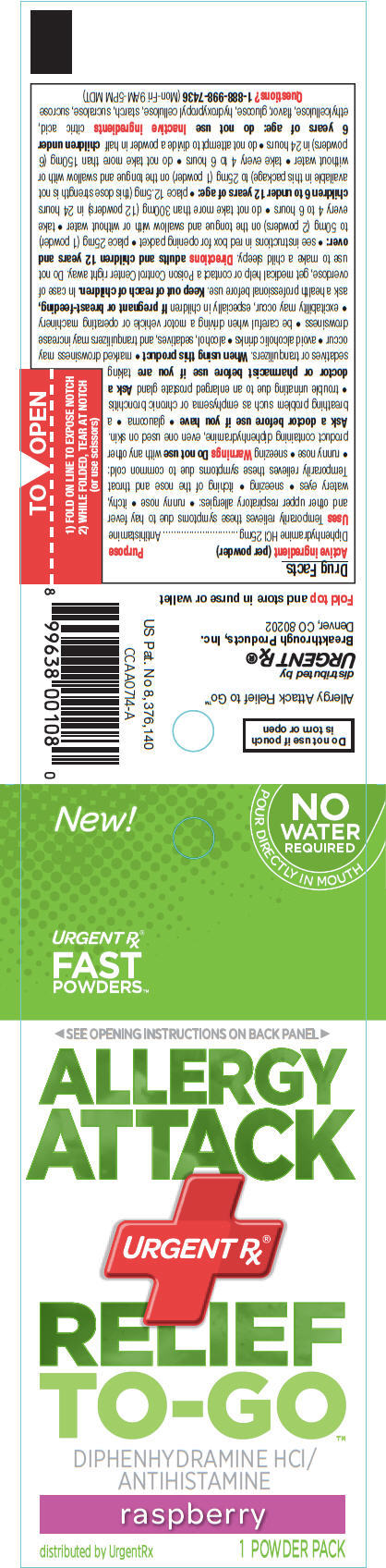 DRUG LABEL: Allergy Attack Relief to Go
NDC: 51596-009 | Form: POWDER
Manufacturer: Breakthrough Products Inc.
Category: otc | Type: HUMAN OTC DRUG LABEL
Date: 20141009

ACTIVE INGREDIENTS: DIPHENHYDRAMINE HYDROCHLORIDE 25 mg/1 1
INACTIVE INGREDIENTS: anhydrous citric acid; ETHYLCELLULOSES; dextrose; HYDROXYPROPYL CELLULOSE (TYPE H); sucralose; sucrose

Allergy Attack Relief to Go™

Drug Facts

Active ingredient (per powder)

Diphenhydramine HCl 25mg

Purpose

Antihistamine

Uses

Temporarily relieves these symptoms due to hay fever and other upper respiratory allergies:

- runny nose
- itchy, watery eyes
- sneezing
- itching of the nose and throat

Temporarily relieves these symptoms due to common cold:

- runny nose
- sneezing

Warnings

Do not use with any other product containing diphenhydramine, even one used on skin.

Ask a doctor before use if you have

- glaucoma
- a breathing problem such as emphysema or chronic bronchitis
- trouble urinating due to an enlarged prostate gland

Ask a doctor or pharmacist before use if you are taking sedatives or tranquilizers.

When using this product

- marked drowsiness may occur
- avoid alcoholic drinks
- alcohol, sedatives, and tranquilizers may increase drowsiness
- be careful when driving a motor vehicle or operating machinery
- excitability may occur, especially in children

PREGNANCY OR BREAST FEEDING

If pregnant or breast-feeding, ask a health professional before use.

Keep out of reach of children. In case of overdose, get medical help or contact a Poison Control Center right away. Do not use to make a child sleepy.

Directions

adults and children 12 years and over:

- see instructions in red box for opening packet
- place 25mg (1 powder) to 50mg (2 powders) on the tongue and swallow with or without water
- take every 4 to 6 hours
- do not take more than 300mg (12 powders) in 24 hours

children 6 to under 12 years of age:

- place 12.5mg (this dose strength is not available in this package) to 25mg (1 powder) on the tongue and swallow with or without water
- take every 4 to 6 hours
- do not take more than 150mg (6 powders) in 24 hours
- do not attempt to divide a powder in half

children under 6 years of age: do not use

Inactive ingredients

citric acid, ethylcellulose, flavor, glucose, hydroxypropyl cellulose, starch, sucralose, sucrose

Questions?

1-888-998-7436 (Mon-Fri 9AM-5PM MDT)

Do not use if pouch
is torn or open

distributed by
URGENT Rx®
Breakthrough Products, Inc.
Denver, CO 80202

PRINCIPAL DISPLAY PANEL - 1 Powder Packet

New!

NO
WATER
REQUIRED
POUR DIRECTLY IN MOUTH

URGENT Rx®
FAST
POWDERS ™

SEE OPENING INSTRUCTIONS ON BACK PANEL

ALLERGY
ATTACK

URGENT Rx®

RELIEF
TO-GO™

DIPHENHYDRAMINE HCl /
ANTIHISTAMINE

raspberry

distributed by UrgentRx
1 POWDER PACK